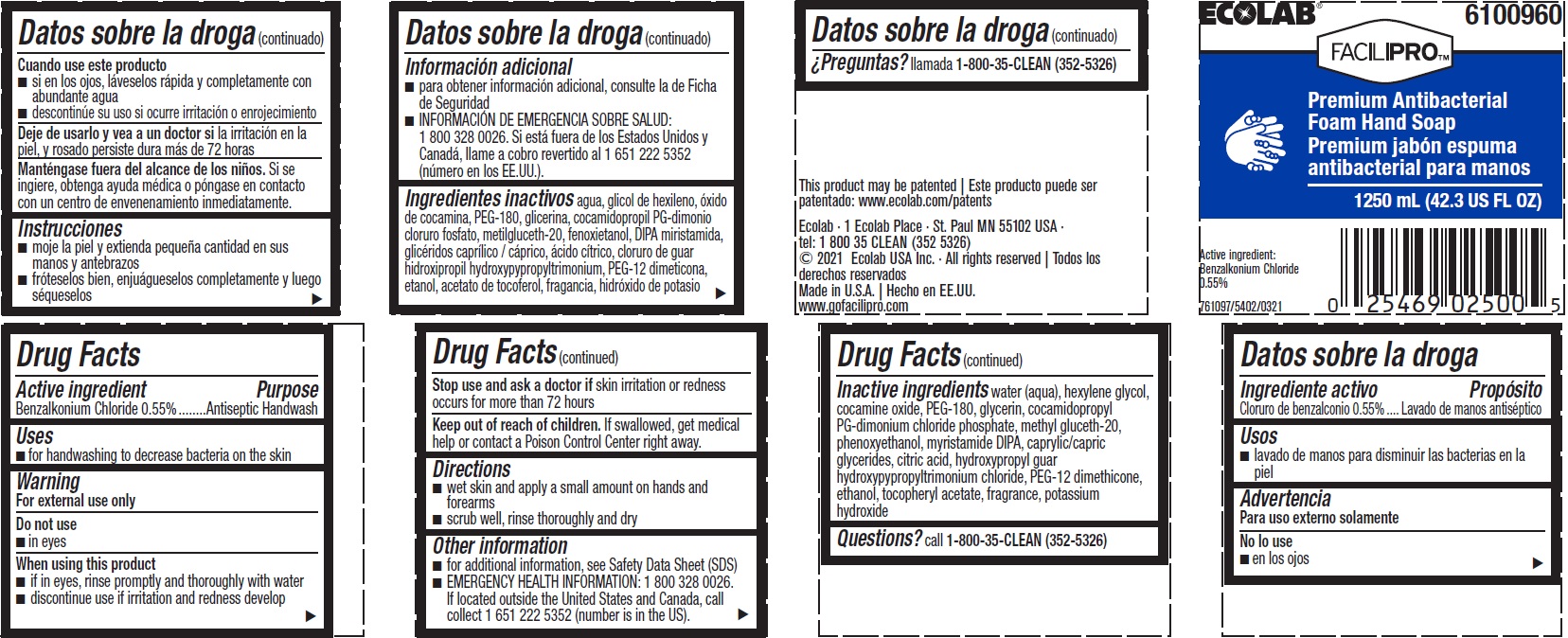 DRUG LABEL: Facilipro
NDC: 47593-565 | Form: SOLUTION
Manufacturer: Ecolab Inc.
Category: otc | Type: HUMAN OTC DRUG LABEL
Date: 20240801

ACTIVE INGREDIENTS: BENZALKONIUM CHLORIDE 5.5 mg/1 mL
INACTIVE INGREDIENTS: WATER; HEXYLENE GLYCOL; COCAMINE OXIDE; POLYETHYLENE GLYCOL 8000; GLYCERIN; COCAMIDOPROPYL PG-DIMONIUM CHLORIDE PHOSPHATE; METHYL GLUCETH-20; PHENOXYETHANOL; MYRISTIC DIISOPROPANOLAMIDE; GLYCERYL MONO- AND DICAPRYLOCAPRATE; ANHYDROUS CITRIC ACID; GUAR GUM; PEG-12 DIMETHICONE (300 CST); ALCOHOL; .ALPHA.-TOCOPHEROL ACETATE; POTASSIUM HYDROXIDE

Drug Facts

Active ingredient

Benzalkonium Chloride 0.55%

Purpose

Antiseptic handwash

Uses

- for handwashing to decrease bacteria on the skin

Warnings

For external use only

Do not use

- In eyes

When using this product

- if in eyes, rinse promptly and thoroughly with water.
- discontinue use if irritation and redness develop.

Stop use and ask a doctor if skin irritation or redness occurs for more than 72 hours

Keep out of reach of children. If swallowed, get medical help or contact a Poison Control Center right away.

Directions

- wet skin and spread a small amount on hands and forearms
- scrub well, rinse thoroughly and dry

Other information

- for additional information, see Safety Data Sheet (SDS)
- EMERGENCY HEALTH INFORMATION: 1 800 328 0026. If located outside the United States and Canada, call collect 1 651 222 5352 (number is in the US).

INACTIVE INGREDIENT

Inactive ingredients water (aqua), hexylene glycol, cocamine oxide, PEG-180, glycerin, cocamidopropyl PG-dimonium chloride phosphate, methyl gluceth-20, phenoxyethanol, myristamide DIPA, caprylic/capric glycerides, citric acid, hydroxypropyl guar hydroxypypropyltrimonium chloride, PEG-12 dimethicone, ethanol, tocopheryl acetate, fragrance, potassium hydroxide

Questions? call 1-800-35-CLEAN (352-5326)

Principal Display Panel and representative label

ECOLAB

6100960

FACILIPRO

Premium Antibacterial

Foam Hand Soap

1250 mL (42.3 US FL OZ)

Active ingredient: Benzalkonium Chloride 0.55%

761097/5402/0321

Ecolab · 1 Ecolab Place · St. Paul MN 55102 USA ·

tel: 1 800 35 CLEAN (352 5326)

© 2021 Ecolab USA Inc. · All rights reserved

Made in U.S.A.

www.gofacilipro.com